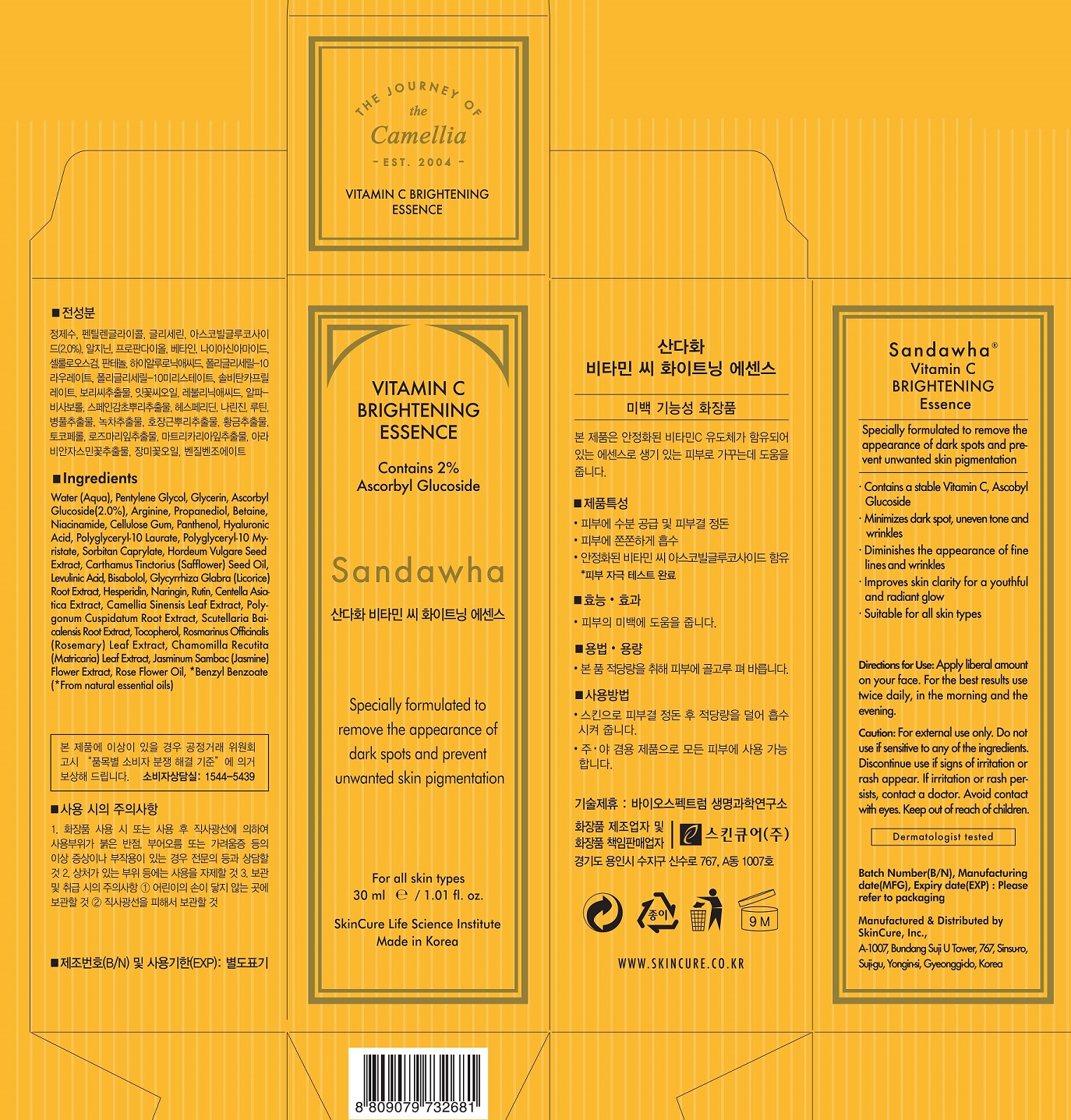 DRUG LABEL: Sandawha Vitamin C Brightening Essence
NDC: 72289-0013 | Form: LIQUID
Manufacturer: SKINCURE INC
Category: otc | Type: HUMAN OTC DRUG LABEL
Date: 20201124

ACTIVE INGREDIENTS: ASCORBYL GLUCOSIDE 2 g/100 mL
INACTIVE INGREDIENTS: PANTHENOL; NIACINAMIDE; WATER

Drug Facts

ACTIVE INGREDIENT

Ascorbyl Glucoside

INACTIVE INGREDIENT

Water (Aqua)
Pentylene Glycol
Glycerin
Arginine
Propanediol
Betaine
Niacinamide
Panthenol
Cellulose Gum
Hyaluronic Acid
Polyglyceryl-10 Myristate
Polyglyceryl-10 Laurate
Sorbitan Caprylate
Hordeum Vulgare Seed Extract
Carthamus Tinctorius (Safflower) Seed Oil
Levulinic Acid
Bisabolol
Glycyrrhiza Glabra (Licorice) Root Extract
Naringin
Rutin
Hesperidin
Centella Asiatica Extract
Polygonum Cuspidatum Root Extract
Tocopherol
Camellia Sinensis Leaf Extract
Scutellaria Baicalensis Root Extract
Rosmarinus Officinalis (Rosemary) Leaf Extract
Chamomilla Recutita (Matricaria) Leaf Extract
Jasminum Sambac (Jasmine) Flower Extract
Rose Flower Oil

PURPOSE

remove the appearance of dark spots and prevent unwanted skin pigmentation

keep out of reach of the children

INDICATIONS AND USAGE

Apply liberal amount on your face. For the best results use twice daily in the morning and the evening.

WARNINGS

for external use only

do not use if sensitive to any of the ingredients

discontinue use if signs of irritation or rash appear

if irritation or rash persists, contact a doctor

DOSAGE AND ADMINISTRATION

for external use only